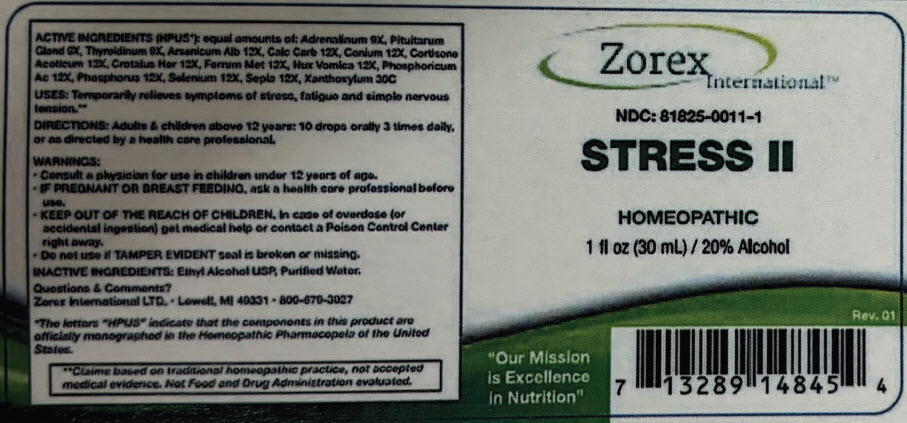 DRUG LABEL: Stress II
NDC: 81825-0011 | Form: LIQUID
Manufacturer: Zorex
Category: homeopathic | Type: HUMAN OTC DRUG LABEL
Date: 20250624

ACTIVE INGREDIENTS: Epinephrine 9 [hp_X]/1 mL; Thyroid, Unspecified 9 [hp_X]/1 mL; BOS TAURUS PITUITARY GLAND, POSTERIOR 9 [hp_X]/1 mL; ARSENIC TRIOXIDE 12 [hp_X]/1 mL; OYSTER SHELL CALCIUM CARBONATE, CRUDE 12 [hp_X]/1 mL; CONIUM MACULATUM FLOWERING TOP 12 [hp_X]/1 mL; CORTISONE ACETATE 12 [hp_X]/1 mL; CROTALUS HORRIDUS HORRIDUS VENOM 12 [hp_X]/1 mL; Iron 12 [hp_X]/1 mL; STRYCHNOS NUX-VOMICA SEED 12 [hp_X]/1 mL; PHOSPHORIC ACID 12 [hp_X]/1 mL; PHOSPHORUS 12 [hp_X]/1 mL; SELENIUM 12 [hp_X]/1 mL; SEPIA OFFICINALIS JUICE 12 [hp_X]/1 mL; ZANTHOXYLUM AMERICANUM BARK 30 [hp_X]/1 mL
INACTIVE INGREDIENTS: Alcohol; Water

Stress II

Drug Facts

ACTIVE INGREDIENT (HPUS [The letters "HPUS" indicate that the components in this product are officially monographed in the Homeopathic Pharmacopeia of the United States.])

equal amounts of: Adrenalinum 9X, Pituitarum Gland 9X, Thyroidium 9X, Arsenicum Alb 12X, Cal Carb 12X, Conium 12X, Cortisone Aceticum 12X, Crotalus Hor 12X, Ferrum Met 12X, Nux Vomica 12X, Phosphoricum Ac 12X, Phosphorus 12X, Selenium 12X, Sepia 12X, Xanthoxylum 30C

USES

PURPOSE

Temporarily relieves symptoms of stress, fatigue and simple nervous tension. [Claims based on traditional homeopathic practice, not accepted medical evidence. Not Food and Drug Administration evaluated.]

DIRECTIONS

Adults & children above 12 years: 10 drops orally 3 times daily, or as directed by a health care professional.

WARNINGS

PREGNANCY OR BREAST FEEDING

- Consult a physician for use in children under the age 12 years of age.
- IF PREGNANT OR BREAST-FEEDING, ask a health care professional before use.

KEEP OUT OF REACH OF CHILDREN

- KEEP OUT OF THE REACH OF CHILDREN. In case of overdose (or accidental ingestion) get medical help or contact Poison Control Center right away.

- Do not use if TAMPER EVIDENT seal is broken or missing.

INACTIVE INGREDIENTS

Ethyl Alcohol USP, Purified Water.

Questions & Comments?

Zorex International LTD. ∙ Lowell, MI 40331 ∙ 800-670-3027

PRINCIPAL DISPLAY PANEL - 30 mL Bottle Label

Zorex
International™

NDC: 81825-0011-1

STRESS II

HOMEOPATHIC
1 fl oz (30 mL) / 20% Alcohol

Rev. 01

"Our Mission
is Excellence
in Nutrition"